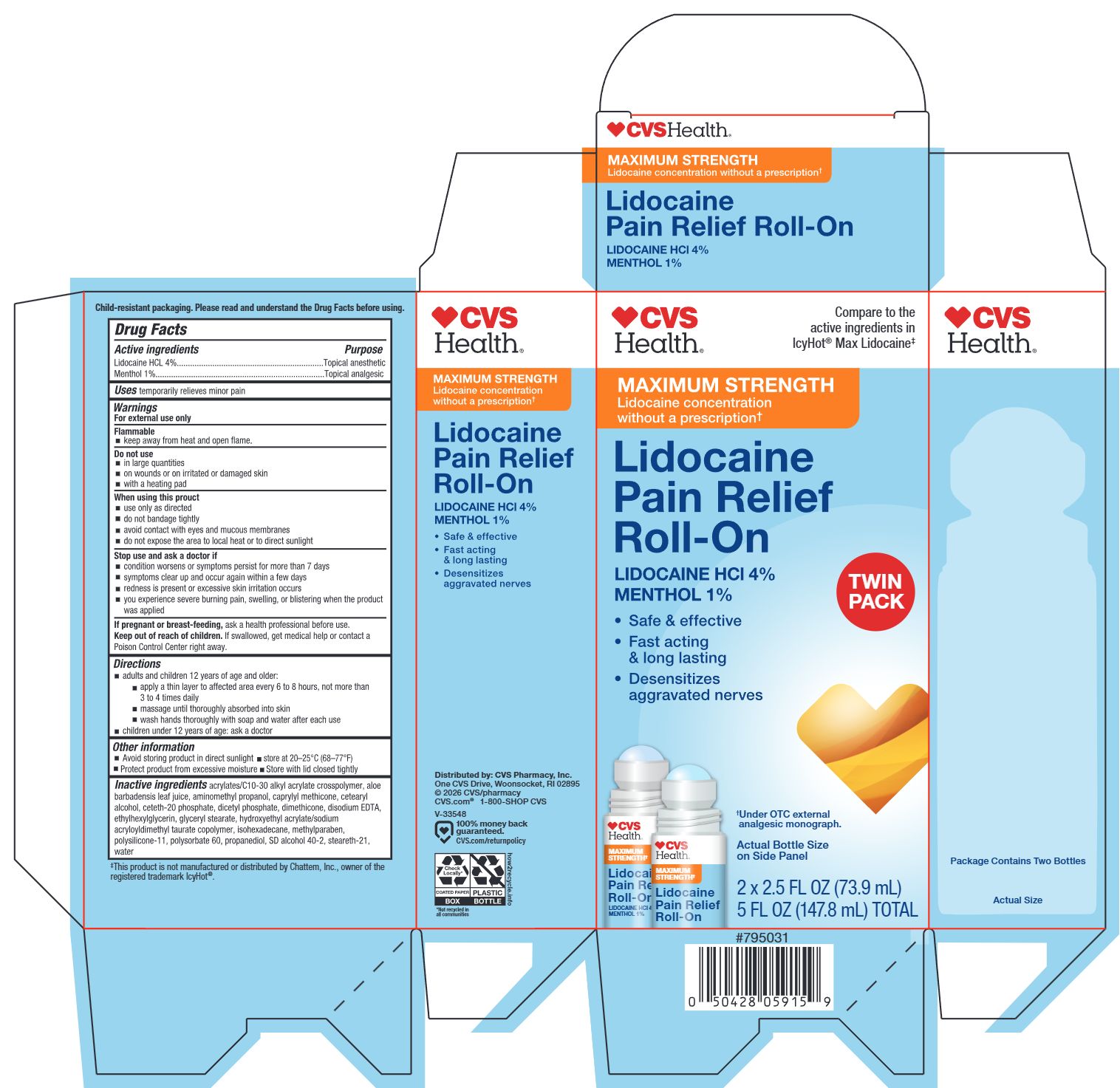 DRUG LABEL: CVS Lidocaine Pain Relief
NDC: 51316-795 | Form: CREAM
Manufacturer: CVS Pharmacy
Category: otc | Type: HUMAN OTC DRUG LABEL
Date: 20260224

ACTIVE INGREDIENTS: MENTHOL, UNSPECIFIED FORM 10 mg/1 mL; LIDOCAINE HYDROCHLORIDE 40 mg/1 mL
INACTIVE INGREDIENTS: ETHYLHEXYLGLYCERIN; CAPRYLYL METHICONE; METHYLPARABEN; CETEARYL ALCOHOL; STEARETH-21; AMINOMETHYL PROPANOL; POLYSORBATE 60; EDETATE DISODIUM; DIMETHICONE/VINYL DIMETHICONE CROSSPOLYMER (SOFT PARTICLE); ACRYLATES/C10-30 ALKYL ACRYLATE CROSSPOLYMER (60000 MPA.S); DICETYL PHOSPHATE; DIMETHICONE; ISOHEXADECANE; HYDROXYETHYL ACRYLATE/SODIUM ACRYLOYLDIMETHYL TAURATE COPOLYMER (45000 MPA.S AT 1%); CETETH-20 PHOSPHATE; ALOE BARBADENSIS LEAF JUICE; ALCOHOL; WATER

CVS Lidocaine Pain Relief Roll-On Twin Pack

Active ingredients

Lidocaine HCl 4%

Menthol 1%

Purposes

Topical anesthetic

Topical analgesic

Uses

temporarily relieves minor pain

Warnings

For external use only

Flammable

- keep away from heat and open flame

Do not use

- in large quantities
- on wounds or on irritated or damaged skin
- with a heating pad

When using this product

- use only as directed
- do not bandage tightly
- avoid contact with eyes and mucous membranes
- do not expose the area to local heat or to direct sunlight

Stop use and ask a doctor if

- condition worsens or symptoms persist for more than 7 days
- symptoms clear up and occur again within a few days
- redness is present of excessive skin irritation occurs
- you experience severe burning pain, swelling, or blistering when the product was applied

If pregnant or breast-feeding,

ask a health professional before use.

Keep out of reach of children.

If swallowed, get medical help or contact a Poison Control Center right away.

Directions

- adults and children 12 years of age and older:
- apply a thin layer to affected area every 6 to 8 hours, not more than 3 to 4 times daily
- massage until thoroughly absorbed into skin
- wash hands thoroughly with soap and water after each use
- children under 12 years of age: ask a doctor

Other information

- avoid storing product in direct sunlight
- store at 20-25°C (68-77°F)
- Protect product from excessive moisture
- Store with lid closed tightly

Inactive ingredients

acrylates/C10-30 alkyl acrylate crosspolymer, aloe barbadensis leaf juice, aminomethyl propanol, caprylyl methicone, cetearyl alcohol, ceteth-20 phosphate, dicetyl phosphate, dimethicone, disodium EDTA, ethylhexylglycerin, glyceryl stearate, hydroxyethyl acrylate/sodium acryloyldimethyl taurate copolymer, isohexadecane, methylparaben, polysilicone-11, polysorbate 60, propanediol, SD Alcohol 40-2, steareth-21, water.

Principal Display Panel - 147.8 mL Total Carton

CVS Health®

Compare to the active ingredeints in IcyHot® Max Lidocaine‡

MAXIMUM STRENGTH

Lidocaine concentration without a prescription†

Lidocaine Pain Relief Roll-On

Lidocaine HCl 4%

Menthol 1%

- Safe & effective
- Fast acting & long lasting
- Desensitizes aggravated nerves

TWIN PACK

†Under OTC external analgesic monograph.

Actual Bottle Size on Side Panel

2 x 2.5 FL OZ (73.9 mL)

5 FL OZ (147.8 mL) TOTAL